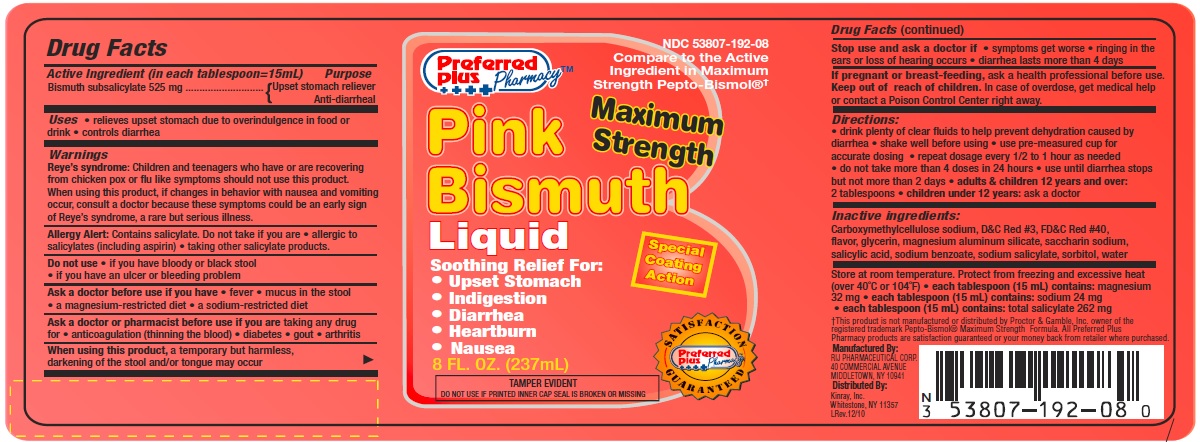 DRUG LABEL: Pink Bismuth Maximum Strength
NDC: 53807-192 | Form: LIQUID
Manufacturer: Rij Pharmaceutical Corporation
Category: otc | Type: HUMAN OTC DRUG LABEL
Date: 20180502

ACTIVE INGREDIENTS: BISMUTH SUBSALICYLATE 525 mg/15 mL
INACTIVE INGREDIENTS: CARBOXYMETHYLCELLULOSE SODIUM; FD&C RED NO. 3; FD&C RED NO. 40; GLYCERIN; MAGNESIUM ALUMINUM SILICATE; SACCHARIN SODIUM; SALICYLIC ACID; SODIUM BENZOATE; SODIUM SALICYLATE; SORBITOL; WATER

Drug Facts

Active ingredient (in each tablespoon= 15 mL)

Bismuth subsalicylate 525 mg

Purpose

Upset stomach reliever and anti-diarrheal

Uses

- relieves upset stomach due to overindulgence in food or drink
- controls diarrhea

Warnings

Reye's syndrome: Children and teenagers who have or are recovering from children pox or flu-like symptoms should not use this product. When using this product, if changes in behavior with nausea and vomiting occur, consult a doctor because these symptoms could be an early sign of Reye's syndrome, a rare but serious illness.

Allergy alert: Contains salicylate. Do not take if you are

- allergic to salicylates (including aspirin)
- taking other salicylate products

Do not use

- if you have bloody or black stool
- if you have an ulcer or bleeding problem

Ask a doctor before use if you have

- fever
- mucus in the stool
- a magnesium-restricted diet
- a sodium-restricted diet

Ask a doctor or pharmacist before use if you are

taking any drug for

- anticoagulation (thinning the blood)
- diabetes
- gout
- arthritis

When using this product

a temporary but harmless, darkening of the stool and/or tongue may occur

Stop use and ask a doctor if

- symptoms get worse
- ringing in the ears or loss of hearing occurs
- diarrhea lasts more than 4 days

If pregnant or breast-feeding,

ask a health professional before use.

Keep out of reach of children.

In case of overdose, get medical help or contact a Poison Control Center right away.

Directions

- drink plenty of clear fluids to help prevent dehydration caused by diarrhea
- shake well before using
- use pre-measured cup for accurate dosing
- repeat dosage every 1/2 to 1 hour as needed
- do not take more than 4 doses in 24 hours
- use until diarrhea stops but not more than 2 days
- adults & children 12 years and over: 2 tablespoons
- children under 12 years: ask a doctor

Inactive ingredients

Carboxymethylcellulose sodium, D&C Red #3, FD&C Red #40, flavor, glycerin, magnesium aluminum silicate, saccharin sodium, salicylic acid, sodium benzoate, sodium saliycylate, sorbitol, water

Other information

- Store at room temperature. Protect from freezing and excessive heat (over 40oF or 104oC)
- each tablespoon (15 mL) contains: magnesium 32 mg
- each tablespoon (15 mL) contains: sodium 24 mg
- each tablespoon (15 mL) contains: total salycylate 262 mg
- TAMPER EVIDENT: DO NOT USE IF PRINTED INNER CAP SEAL IS BROKEN OR MISSING.